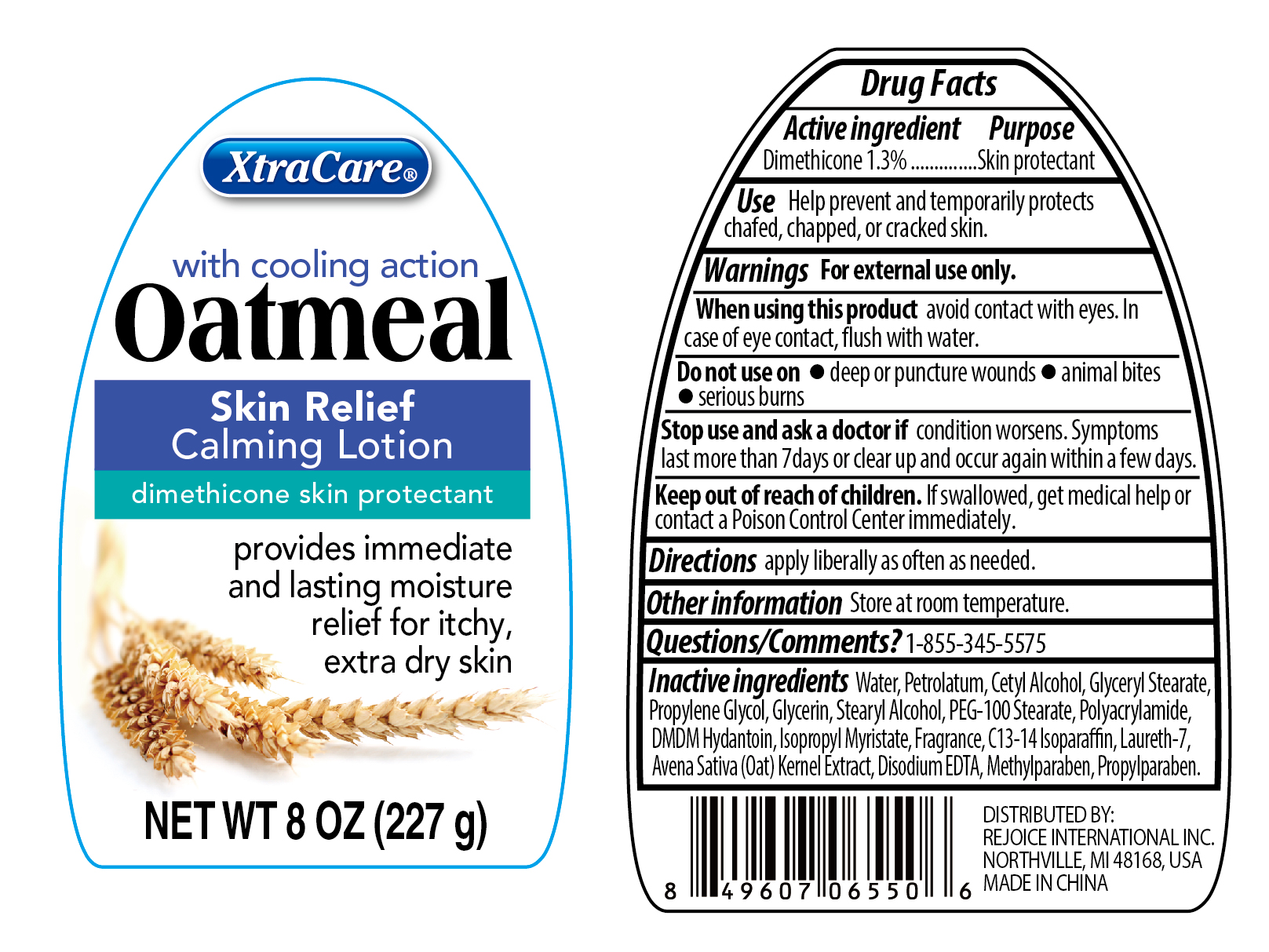 DRUG LABEL: Oatmeal Skin Relief Calming .
NDC: 57337-100 | Form: LOTION
Manufacturer: Rejoice International Inc.
Category: otc | Type: HUMAN OTC DRUG LABEL
Date: 20190307

ACTIVE INGREDIENTS: DIMETHICONE 3 g/227 g
INACTIVE INGREDIENTS: CETYL ALCOHOL; ISOPROPYL MYRISTATE; LAURETH-7; MAGNESIUM DISODIUM EDTA; POLYACRYLAMIDE (10000 MW); C13-14 ISOPARAFFIN; CETYL STEARATE; PEG-100 STEARATE; DMDM HYDANTOIN; METHYLPARABEN; WATER; PETROLATUM; GLYCERIN; PROPYLENE GLYCOL; STEARYL ALCOHOL; OAT KERNEL OIL; DISTEARYLDIMONIUM CHLORIDE

Oatmeal daily moisturizing lotion (8 oz.)

Active Ingredient

Dimethicone 1.3%

Purpose

Skin protectant

Keep out of reach of children. If swallowed, get medical help or contact a Poison Control Center immediately.

Use

Help prevent and temporarily protects chafed, chapped, or cracked skin.

Warnings For external use only.

When using this product avoid contact with eyes. In case of eye contact, flush with water.

Do not use on

Deep or puncture wounds
Animal bites
Serious burns

Stop use and ask a doctor if conditions worsens. Symptoms last more than 7 days or clear up and occur again within a few days.

DOSAGE AND ADMINISTRATION

Directions apply liberally as often as needed.

Other Information store at room temperature.

Inactive Ingredients

Water, Petrolatum, Cetyl Alcohol, Glyceryl Stearate, Propylene Glycol, Glycerin, Stearyl Alcohol, PEG-100 Stearate, Polyacrylamide, DMDM Hydrantoin, Isopropyl Myristate, Fragrance, C13-14 Isoparaffin, Laureth-7, Avena Sativa (Oat) Kernel Extract, Disodium EDTA, Methylparaben, Propylparaben